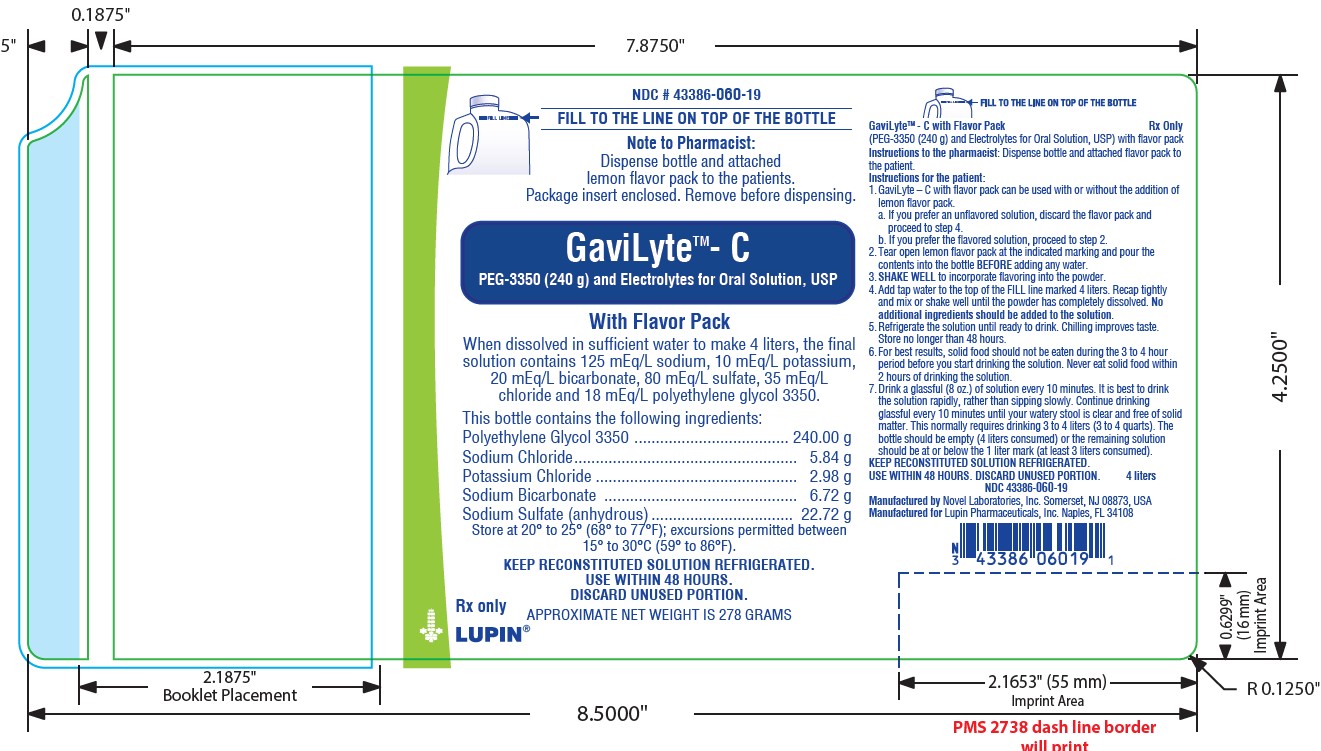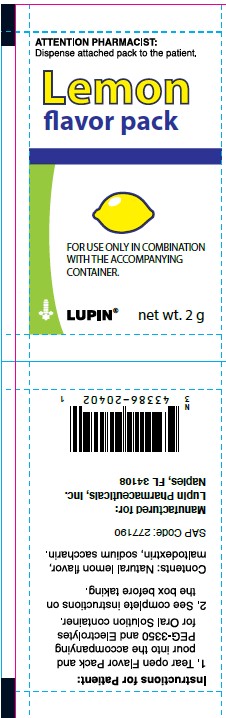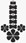 DRUG LABEL: GaviLyte - C
NDC: 43386-060 | Form: POWDER, FOR SOLUTION
Manufacturer: Lupin Pharmaceuticals,Inc.
Category: prescription | Type: HUMAN PRESCRIPTION DRUG LABEL
Date: 20250910

ACTIVE INGREDIENTS: POLYETHYLENE GLYCOL 3350 240 g/278.26 g; SODIUM CHLORIDE 5.84 g/278.26 g; POTASSIUM CHLORIDE 2.98 g/278.26 g; SODIUM BICARBONATE 6.72 g/278.26 g; SODIUM SULFATE ANHYDROUS 22.72 g/278.26 g
INACTIVE INGREDIENTS: SACCHARIN SODIUM; MALTODEXTRIN

GaviLyte&trade;-C with Flavor Pack
(PEG-3350 (240 g) and Electrolytes for Oral Solution, USP) with flavor pack

DESCRIPTION

GaviLyte- C with flavor pack is a white, colon lavage preparation provided as water-soluble components for solution. In solution this preparation with lemon flavor pack added delivers the following, in grams per liter.

Polyethylene glycol 3350 240.00

Sodium chloride 5.84

Potassium chloride 6.72

Sodium bicarbonate 2.98

Sodium sulfate 22.72

Flavor ingredients 0.500

When dissolved in sufficient water to make 4 liters, the final solution contains 125 mEq/L sodium, 10 mEq/L potassium, 20 mEq/L bicarbonate, 80 mEq/L sulfate, 35 mEq/L chloride and 18 mEq/L polyethylene glycol 3350. The reconstituted solution is an isosmotic solution, for oral administration, having mild salty taste. This preparation can be used without the lemon flavor pack and is administered orally or via nasogastric tube.

Each lemon flavor pack (2 g) contains natural lemon flavor powder, saccharin sodium, maltodextrin.

CLINICAL PHARMACOLOGY

GaviLyte- C with flavor pack cleanses the bowel by induction of diarrhea. The osmotic activity of polyethylene glycol 3350, in combination with the electrolyte concentration, results in virtually no net absorption or excretion of ions or water. Accordingly, large volumes may be administered without significant changes in fluid and electrolyte balance.

INDICATIONS AND USAGE

GaviLyte- C with flavor pack is indicated for bowel cleansing prior to colonoscopy or barium enema X-ray examination.

CONTRAINDICATIONS

GaviLyte- C with flavor pack is contraindicated in patients known to be hypersensitive to any of the components. GaviLyte- C with flavor pack is contraindicated in patients with ileus, gastrointestinal obstruction, gastric retention, bowel perforation, toxic colitis or toxic megacolon.

WARNINGS

Flavor pack is for use only in combination with the contents of the accompanying 4 liter container. No other additional ingredients (e.g., flavorings) should be added to the solution. GaviLyte- C with flavor pack should be used with caution in patients with severe ulcerative colitis.

PRECAUTIONS

General

Patients with impaired gag reflex, unconscious or semiconscious patients and patients prone to regurgitation or aspiration should be observed during the administration of GaviLyte- C with flavor pack, especially if it is administered via nasogastric tube.

If gastrointestinal obstruction or perforation is suspected appropriate studies should be performed to rule out these conditions before administration of GaviLyte- C with flavor pack.

INFORMATION FOR PATIENTS

GaviLyte- C with flavor pack produces a watery stool which cleanses the bowel prior to examination.

For best results, no solid food should be ingested during the 3 to 4 hour period prior to the initiation of GaviLyte- C with flavor pack administration. In no case should solid foods be eaten within 2 hours of drinking GaviLyte- C with flavor pack. The rate of administration is 240 mL (8 fl. oz.) every 10 minutes. Rapid drinking of each portion is preferred rather than drinking small amounts continuously. The first bowel movement should occur approximately one hour after the start of GaviLyte- C with flavor pack administration.

Administration of GaviLyte- C with flavor pack should be continued until the watery stool is clear and free of solid matter. This normally requires the consumption of approximately 3 to 4 liters (3 to 4 quarts), although more or less may be required in some patients. The unused portion should be discarded.

DRUG INTERACTIONS

Oral medication administered within one hour of start of administration of GaviLyte- C with flavor pack may be flushed from the gastrointestinal tract and not absorbed.

CARCINOGENESIS, MUTAGENESIS, IMPAIRMENT OF FERTILITY

Studies to evaluate carcinogenic or mutagenic potential or potential to adversely affect male or female fertility have not been performed.

PREGNANCY

Category C. Animal reproduction studies have not been conducted with GaviLyte- C with flavor pack, and it is not known whether GaviLyte- C with flavor pack can affect reproductive capacity or harm the fetus when administered to a pregnant patient. GaviLyte- C with flavor pack should be given to a pregnant patient only if clearly needed.

PEDIATRIC USE

Safety and effectiveness in pediatric patients have not been established.

GERIATRIC USE

Published literature contains isolated reports of serious adverse reactions following the administration of PEG-ELS products in patients over 60 years of age. These adverse events include upper GI bleeding from Mallory-Weiss Tear, esophageal perforation, asystole, sudden dyspnea with pulmonary edema, and "butterfly-like" infiltrate on chest x-ray after vomiting and aspirating PEG.

ADVERSE REACTIONS

Nausea, abdominal fullness and bloating are the most frequent adverse reactions, occurring in up to 50% of patients. Abdominal cramps, vomiting and anal irritation occur less frequently. These adverse reactions are transient. Isolated cases of urticaria, rhinorrhea, dermatitis, and rarely anaphylaxis, angioedema, tongue edema, and face edema have been reported which may represent allergic reactions.

DOSAGE AND ADMINISTRATION

GaviLyte- C with flavor pack can be administered orally or by nasogastric tube. Patients should fast at least 3 hours prior to administration. A one hour waiting period after the appearance of clear liquid stool should be allowed prior to examination to complete bowel evacuation. No foods except clear liquids should be permitted prior to examination after GaviLyte- C with flavor pack administration.

ORAL: The recommended adult oral dose is 240 mL (8 fl. oz.) every 10 minutes (see INFORMATION FOR PATIENTS). Lavage is complete when fecal discharge is clear. Lavage is usually complete after the ingestion of 3 to 4 liters.

NASOGASTRIC TUBE: GaviLyte- C with flavor pack is administered at a rate of 20 to 30 mL per minute (1.2 to 1.8 L/hour).

PREPARATION OF GaviLyte- C with flavor pack SOLUTION: This preparation can be used with or without the lemon flavor pack.

1. To add flavor, tear open lemon flavor pack at the indicated marking and pour contents into the bottle BEFORE reconstitution.

2. SHAKE WELL to incorporate flavoring into the powder.

3. Add tap water to FILL line. Replace cap tightly and mix or shake well until all ingredients have dissolved. (No other additional ingredients, e.g. flavorings, should be added to the solution.)

Note: If not using flavor pack, omit steps one and two, above.

HOW SUPPLIED

GaviLyte- C with flavor pack is supplied in 4 liter bottles with an attached lemon flavor pack. Each 4 liter bottle contains polyethylene glycol-3350 240 g, sodium chloride 5.84 g, potassium chloride 2.98 g, sodium bicarbonate 6.72 g, sodium sulfate (anhydrous) 22.72 g. This preparation is supplied in powdered form, for oral administration as a solution.

GaviLyte- C with flavor pack 4liter: NDC 43386-060-19

Store at 20° to 25°C (68° to 77°F): excursions permitted between 15° to 30°C (59° to 86°F).

KEEP RECONSTITUTED SOLUTION REFRIGERATED. USE WITHIN 48 HOURS. DISCARD UNUSED PORTION.

LUPIN and the are registered trademarks of Lupin Pharmaceuticals, Inc.

Manufactured by:

Novel Laboratories, Inc.

Somerset, NJ 08873, USA

Manufactured for:

Lupin Pharmaceuticals, Inc.

Naples FL, 34108

SAP Code: 278922

Rev. 11/2024

PACKAGE LABEL.PRINCIPAL DISPLAY PANEL

Gavilyte-C with Flavor Pack (PEG-3350 (240g) and electrolytes for oral solution, USP) with flavor pack

Label

Lemon Flavor Pack